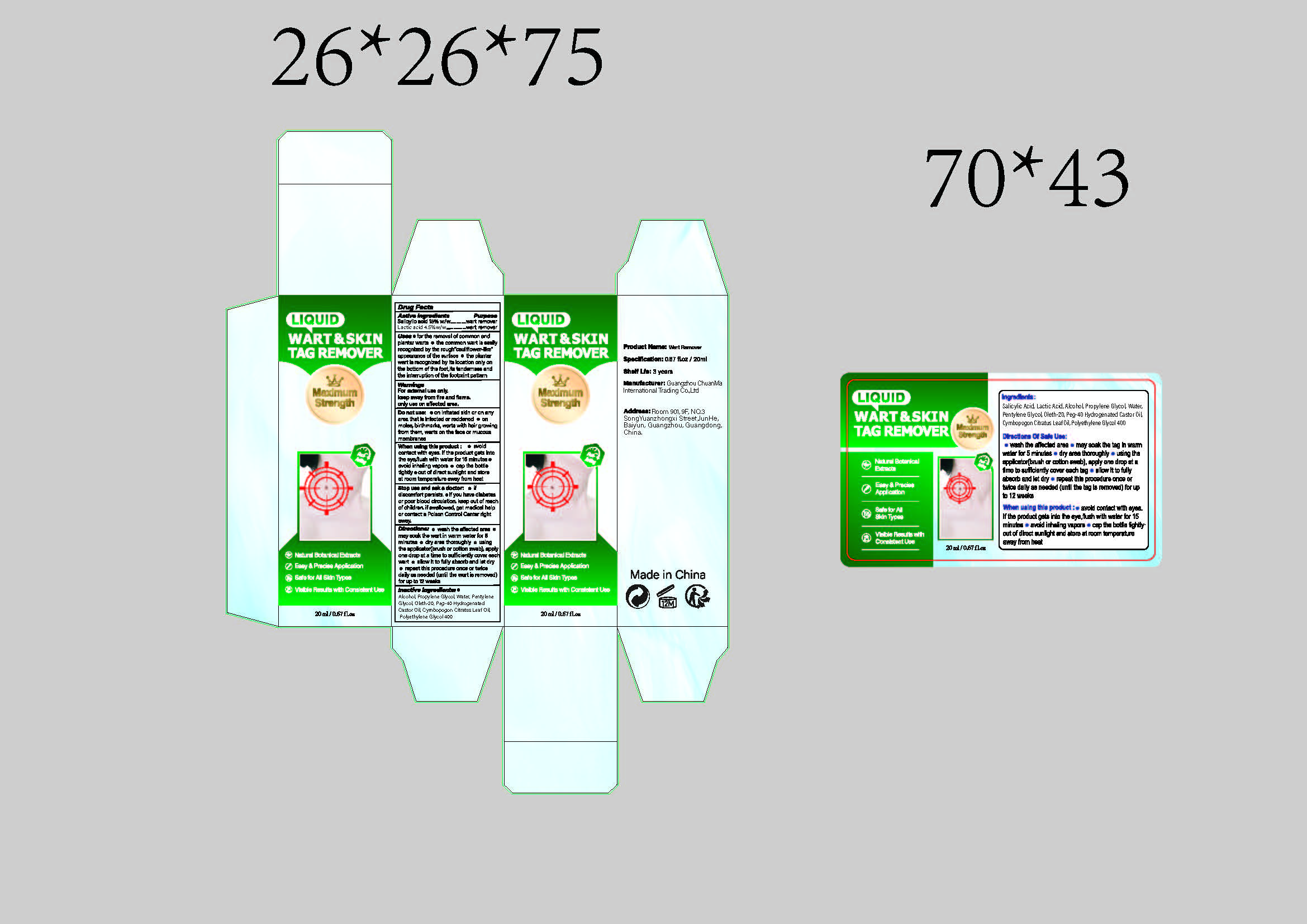 DRUG LABEL: WART SKIN TAG REMOVER
NDC: 85593-101 | Form: LIQUID
Manufacturer: Guangzhou ChuanMa International Trading Co.,Ltd.
Category: otc | Type: HUMAN OTC DRUG LABEL
Date: 20250720

ACTIVE INGREDIENTS: SALICYLIC ACID 15 g/100 mL; LACTIC ACID 4.5 g/100 mL
INACTIVE INGREDIENTS: CYMBOPOGON CITRATUS LEAF OIL; PROPYLENE GLYCOL; POLYOXYL 40 HYDROGENATED CASTOR OIL; POLYETHYLENE GLYCOL 400; WATER; PENTYLENE GLYCOL; OLETH-20; ALCOHOL

ACTIVE INGREDIENT

SALICYLIC ACID 15.00%
LACTIC ACID 4.50%

PURPOSE

Wart remover

When using this product:e avoidcontact with eyes. lf the product gets intothe eye,flush with water for 15 minutes avoid inhaling vapors o cap the bottletightly e out of direct sunlight and storeat room temperature away from heat

DOSAGE AND ADMINISTRATION

wash the affected areamay soak the wart in warm water for 5minutes e dry area thoroughly e usingthe applicator(brush or cotton swab), applyone drop at a time to sufficiently cover eachwart e allow it to fully absorb and let dryrepeat this procedure once or twicedaily as needed (until the wart is removed)for up to 12 weeks

INDICATIONS AND USAGE

for the removal of common andplantar warts o the common wart is easilyrecognized by the rough"cauliflower-like"appearance of the surface o the plantarwart is recognized by its location only onthe bottom of the foot,its tenderness andthe interruption of the footprint pattern

WARNINGS

WarningsFor external use only.keep away from fire and flame.only use on affected area.

Do not use: on irritated skin or on anyarea that is infected or reddened o onmoles, birthmarks, warts with hair growingfrom them, warts on the face or mucousmembranes

KEEP OUT OF REACH OF CHILDREN

keep out of reachof children, if swallowed, get medical helpor contact a Poison Control Center rightaway.

INACTIVE INGREDIENT

Inactive ingredients: ®Alcohol, Propylene Glycol, Water, PentyleneGlycol, Oleth-20, Peg-40 HydrogenatedCastor Oil, Cymbopogon Citratus Leaf Oil,Polyethylene Glycol 400